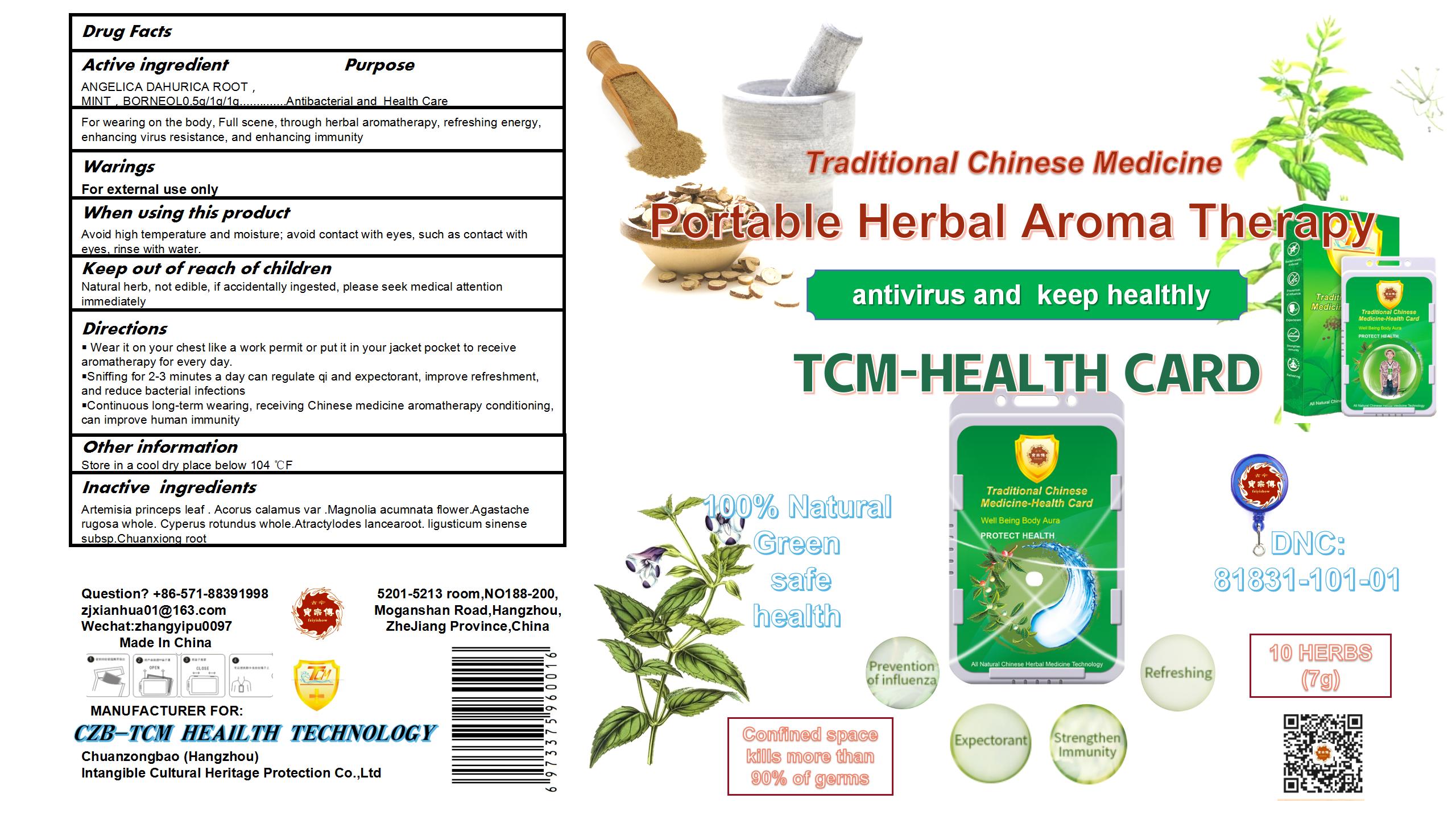 DRUG LABEL: Traditional Chinese Medicine Health Card and TCM Epidemic Prevention Card
NDC: 81831-101 | Form: POWDER
Manufacturer: Chuanzongbao (Hangzhou) intangible cultural heritage protection Co., Ltd
Category: otc | Type: HUMAN OTC DRUG LABEL
Date: 20250909

ACTIVE INGREDIENTS: BORNEOL 1 g/6.5 g; MINT 1 g/6.5 g; ANGELICA DAHURICA ROOT 0.5 g/6.5 g
INACTIVE INGREDIENTS: AGASTACHE RUGOSA WHOLE; CYPERUS ROTUNDUS WHOLE; ARTEMISIA PRINCEPS LEAF; LIGUSTICUM SINENSE SUBSP. CHUANXIONG ROOT; ACORUS CALAMUS VAR. ANGUSTATUS WHOLE; MAGNOLIA ACUMINATA FLOWER; ATRACTYLODES LANCEA ROOT

Traditional Chinese Medicine Health Card and TCM Epidemic Prevention Card

Traditional Chinese Medicine Health Card and TCM Epidemic Prevention Card

Active Ingredient(s)

ANGELICA DAHURICA ROOT 0.5g/6.5g
MINT 1g/6.5g
BORNEOL 1g/6.5g

Purpose

Antibacterial and Health Care

Use

For wearing on the body, Full scene, through herbal aromatherapy, refreshing energy, enhancing virus resistance, and enhancing immunity

Warnings

For external use only.

WHEN USING

Avoid high temperature and moisture; avoid contact with eyes, such as contact with eyes, rinse with water.

Keep out of reach of children. Natural herb, not edible, if accidentally ingested, please seek medical attention immediately

Directions

- Wear it on your chest like a work permit or put it in your jacket pocket to receive aromatherapy for every day.
- Sniffing for 2-3 minutes a day can regulate qi and expectorant, improve refreshment, and reduce bacterial infections
- Continuous long-term wearing, receiving Chinese medicine aromatherapy conditioning, can improve human immunity

Other information

- Store in a cool dry place below 104 ℃F

Inactive ingredients

ARTEMISIA PRINCEPS LEAF
ACORUS CALAMUS VAR. ANGUSTATUS WHOLE
MAGNOLIA ACUMINATA FLOWER
AGASTACHE RUGOSA WHOLE
CYPERUS ROTUNDUS WHOLE
ATRACTYLODES LANCEA ROOT
LIGUSTICUM SINENSE SUBSP. CHUANXIONG ROOT